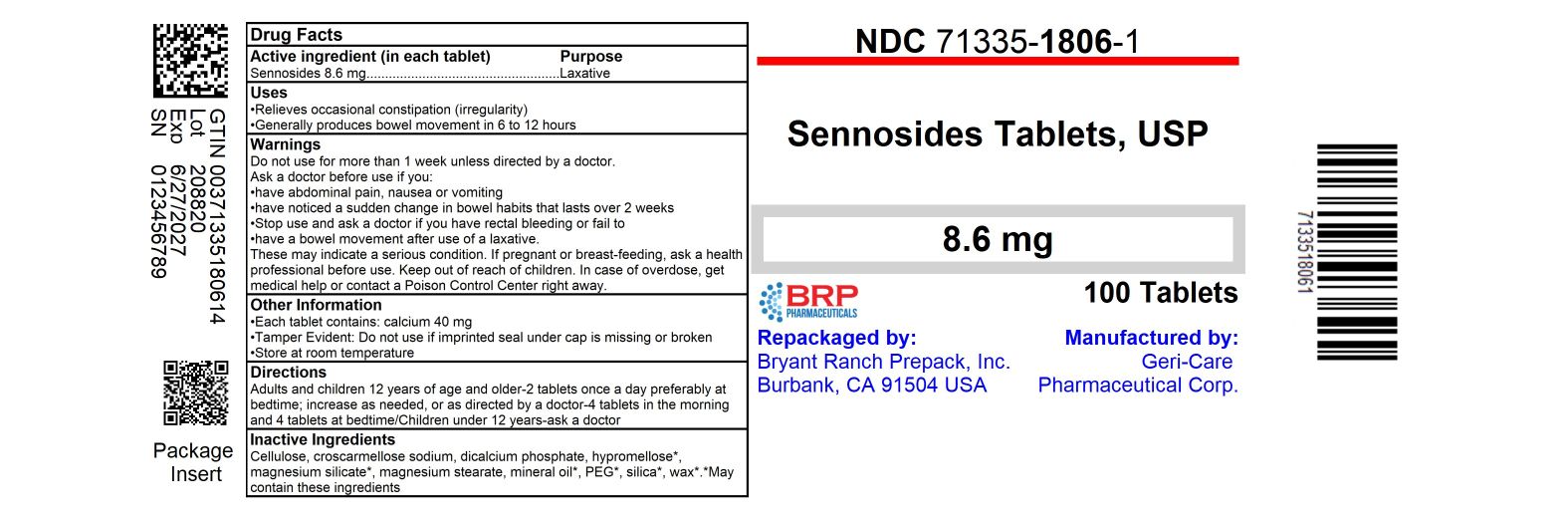 DRUG LABEL: Geri-kot
NDC: 71335-1806 | Form: TABLET
Manufacturer: Bryant Ranch Prepack
Category: otc | Type: HUMAN OTC DRUG LABEL
Date: 20250627

ACTIVE INGREDIENTS: SENNOSIDES 8.6 mg/1 1
INACTIVE INGREDIENTS: SILICON DIOXIDE; MICROCRYSTALLINE CELLULOSE; CROSCARMELLOSE SODIUM; ANHYDROUS DIBASIC CALCIUM PHOSPHATE; MAGNESIUM SILICATE; MAGNESIUM STEARATE; MINERAL OIL; POLYETHYLENE GLYCOL, UNSPECIFIED; HYPROMELLOSE, UNSPECIFIED; CARNAUBA WAX

gc 454

Active ingredient (in each tablet)

Sennosides 8.6 mg

Purpose

Laxative

Uses

- relieves occasional constipation (irregularity)

- generally produces bowel movement in 6 to 12 hours

Warnings

Do not use

for more than 1 week unless directed by a doctor.

Ask a doctor before use if you

- have abdominal pain, nausea or vomiting
- have noticed a sudden change in bowel habits that lasts over 2 weeks

Stop use and ask a doctor if you have rectal bleeding or fail to
have a bowel movement after use of a laxative.
These may indicate a serious condition .

If pregnant or breast-feeding,

ask a health professional before use.

Keep out of reach of children. In case of overdose, get medical help or contact a Poison Control Center right away.

Directions

• do not exceed 8 tablets in 24 hours

Age | Starting Dose | Maximum Dose
adults and children 12 years of age and older | 2 tablets once a day preferably at bedtime; increase as needed, or as directed by a doctor | 4 tablets in the morning and 4 tablets at bedtime
children under 12 years | ask a doctor

Other information

- each tablet contains: calcium 40 mg
- Tamper Evident: Do not use if imprinted seal under cap is missing or broken
- store at room temperature

Inactive ingredients

cellulose, croscarmellose sodium,
dicalcium phosphate, hypromellose*, magnesium silicate*,
magnesium stearate, mineral oil*, PEG*, silica*, wax*.
*May contain these ingredients

HOW SUPPLIED

Sennosides 8.6mg Tablet

- NDC 71335-1806-1: 100 Tablets in a BOTTLE
- NDC 71335-1806-2: 60 Tablets in a BOTTLE
- NDC 71335-1806-3: 120 Tablets in a BOTTLE
- NDC 71335-1806-4: 56 Tablets in a BOTTLE
- NDC 71335-1806-5: 30 Tablets in a BOTTLE
- NDC 71335-1806-6: 90 Tablets in a BOTTLE
- NDC 71335-1806-7: 10 Tablets in a BOTTLE

Repackaged/Relabeled by:
Bryant Ranch Prepack, Inc.
Burbank, CA 91504

PACKAGE LABEL

Sennosides 8.6mg Tablet